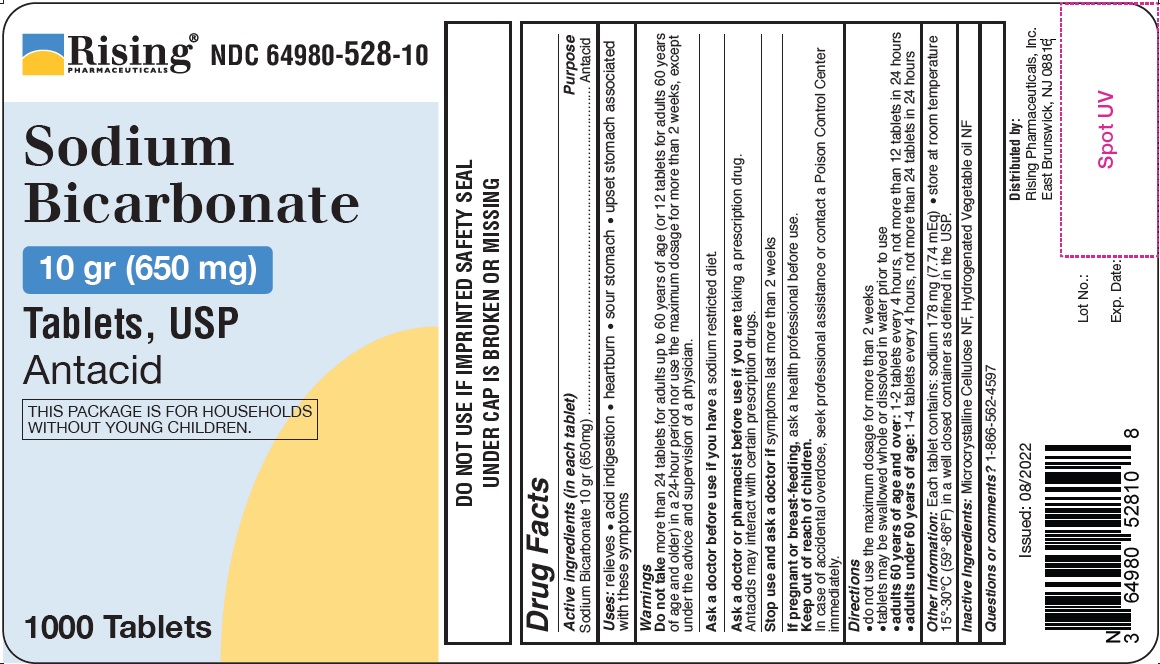 DRUG LABEL: Sodium Bicarbonate
NDC: 64980-528 | Form: TABLET
Manufacturer: Rising Pharma Holdings, Inc.
Category: otc | Type: Human OTC Drug Label
Date: 20241101

ACTIVE INGREDIENTS: SODIUM BICARBONATE 650 mg/1 1
INACTIVE INGREDIENTS: MICROCRYSTALLINE CELLULOSE; CORN OIL

Sodium Bicarbonate 10 gr (650 mg) Tablets, USP
Antacid

DO NOT USE IF IMPRINTED SAFETY SEAL UNDER CAP IS BROKEN OR MISSING

Drug Facts
Active ingredients (in each tablet)
Sodium Bicarbonate 10 gr (650 mg)

Purpose
Antacid

INDICATIONS AND USAGE

Uses: relieves • acid indigestion • heartburn • sour stomach • upset stomach associated with these symptoms

Warnings
Do not take more than 24 tablets for adults up to 60 years of age (or 12 tablets for adults 60 years of age and older) in a 24-hour period nor use the maximum dosage for more than 2 weeks, except under the advice and supervision of a physician.
Ask a doctor before use if you have a sodium restricted diet.
Ask a doctor or pharmacist before use if you are taking a prescription drug.
Antacids may interact with certain prescription drugs.
Stop use and ask a doctor if symptoms last more than 2 weeks
If pregnant or breast-feeding, ask a health professional before use.

Keep out of reach of children.
In case of accidental overdose, seek professional assistance or contact a Poison Control Center immediately.

Directions

- do not use the maximum dosage for more than 2 weeks
- tablets may be swallowed whole or dissolved in water prior to use
- adults 60 years of age and over: 1-2 tablets every 4 hours, not more than 12 tablets in 24 hours
- adults under 60 years of age: 1-4 tablets every 4 hours, not more than 24 tablets in 24 hours

Other Information: Each tablet contains: sodium 178 mg (7.74 mEq) • store at room temperature 15°-30°C (59°-86°F) in a well closed container as defined in the USP.

INACTIVE INGREDIENT

Inactive Ingredients: Microcrystalline cellulose NF, Hydrogenated Vegetable oil NF

Questions or Comments? 1-866-562-4597

Issued: 08/2022
Distributed by:
Rising Pharmaceuticals, Inc.
East Brunswick, NJ 08816

PACKAGE LABEL

———PRINCIPAL DISPLAY PANEL———

Rising Pharmaceuticals Inc. NDC 64980-528-10

Sodium Bicarbonate 10 gr (650 mg) TABLETS, USP
Antacid

THIS PACKAGE IS FOR HOUSEHOLDS WITHOUT YOUNG CHILDREN.

1000 Tablets